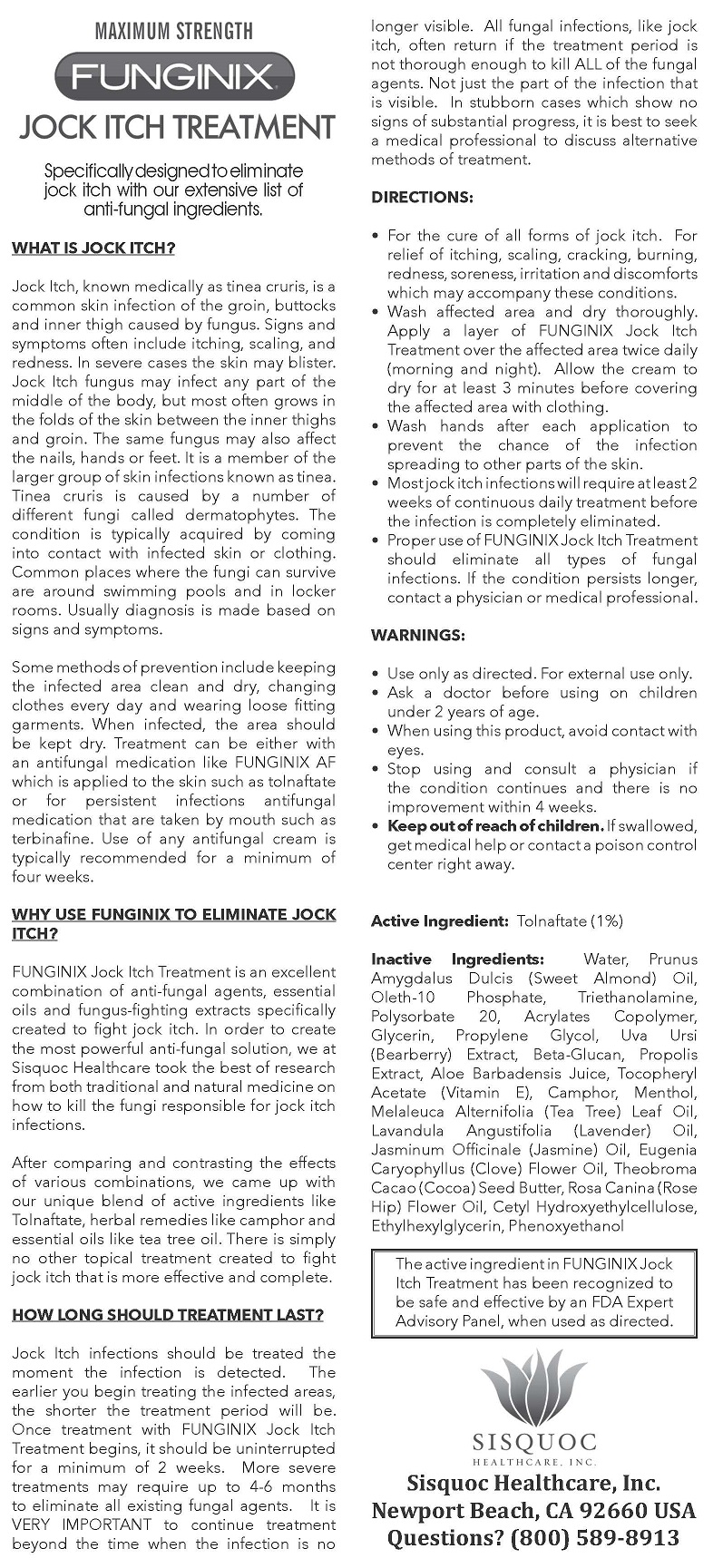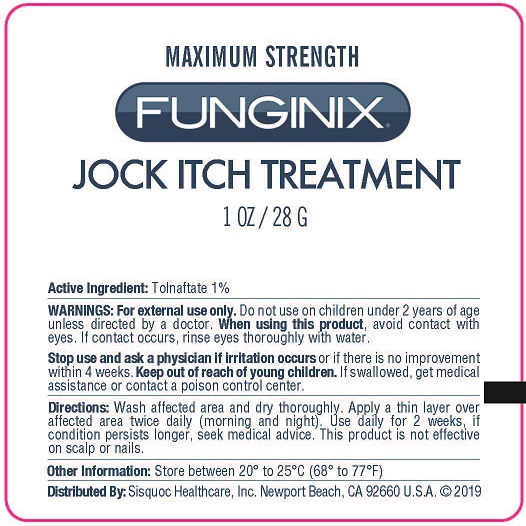 DRUG LABEL: FUNGINIX JOCK ITCH TREATMENT
NDC: 71229-104 | Form: CREAM
Manufacturer: The Sisquoc Healthcare Corporation
Category: otc | Type: HUMAN OTC DRUG LABEL
Date: 20250225

ACTIVE INGREDIENTS: TOLNAFTATE 1 g/100 g
INACTIVE INGREDIENTS: WATER; ALMOND OIL; OLETH-10 PHOSPHATE; TROLAMINE; POLYSORBATE 20; BUTYL ACRYLATE/METHYL METHACRYLATE/METHACRYLIC ACID COPOLYMER (18000 MW); GLYCERIN; PROPYLENE GLYCOL; ARCTOSTAPHYLOS UVA-URSI WHOLE; OAT; PROPOLIS WAX; ALOE VERA LEAF; .ALPHA.-TOCOPHEROL ACETATE; CAMPHOR OIL; MENTHOL; TEA TREE OIL; LAVANDULA ANGUSTIFOLIA WHOLE; JASMINUM OFFICINALE WHOLE; CLOVE LEAF OIL; COCOA BUTTER; ROSA CANINA FRUIT OIL; CETYL HYDROXYETHYLCELLULOSE (350000 MW); ETHYLHEXYLGLYCERIN; PHENOXYETHANOL

Sisquoc HC (as PLD) - FUNGINIX JOCK ITCH TREATMENT (71229-104)

ACTIVE INGREDIENT

TOLNAFTATE 1%

PURPOSE

ANTIFUNGAL

USES

- ANTI-FUNGAL TREATMENT

WARNINGS

FOR EXTERNAL USE ONLY.

DO NOT USE ON CHILDREN UNDER 2 YEARS OF AGE UNLESS DIRECTED BY A DOCTOR.

WHEN USING THIS PRODUCT AVOID CONTACT WITH THE EYES. IF CONTACT OCCURS, RINSE THE EYES VERY THOROUGHLY WITH WATER.

STOP USE AND ASK A DOCTOR IF IRRITATION OCCURS OR THERE IS NO IMPROVEMENT WITHIN 4 WEEKS.

KEEP OUT OF REACH OF CHILDREN. IF SWALLOWED, GET MEDICAL HELP OR CONTACT A POISON CONTROL CENTER RIGHT AWAY.

DIRECTIONS

- For the cure of all forms of jock itch. For relief of itching, scaling, cracking, burning, redness, soreness, irritation and discomforts which may accompany these conditions.
- Wash affected area and dry thoroughly. Apply a layer of FUNGINIX Jock Itch Treatment over the affected area twice daily (morning and night). Allow the cream to dry for at least 3 minutes before covering the affected area with clothing.
- Wash hands after each application to prevent the chance of the infection spreading to other parts of the skin.
- Most jock itch infections will require at least 2 weeks of continuous daily treatment before the infection is completely eliminated.
- Proper use of FUNGINIX Jock Itch Treatment should eliminate all types of fungal infections. If the condition persists longer, contact a physician or medical professional.

INACTIVE INGREDIENTS

Water, Prunus Amygdalus Dulcis (Sweet Almond) Oil, Oleth-10 Phosphate, Triethanolamine, Polysorbate 20, Acrylates Copolymer, Glycerin,
Propylene Glycol, Uva Ursi (Bearberry) Extract, Beta-Glucan, Propolis Extract, Aloe Barbadensis Juice, Tocopheryl Acetate (Vitamin E), Camphor, Menthol, Melaleuca Alternifolia (Tea Tree) Leaf Oil, Lavandula Angustifolia (Lavender) Oil, Jasminum Oficinale (Jasmine) Oil, Eugenia Caryophyllus (Clove) Flower Oil, Theobroma Cacao (Cocoa) Seed Butter, Rosa Canina (Rose Hip) Flower Oil, Cetyl Hydroxyethylcellulose, Ethylhexylglycerin, Phenoxyethanol

STORAGE AND HANDLING

Store between 20°c to 25°C (68° to 77°F)